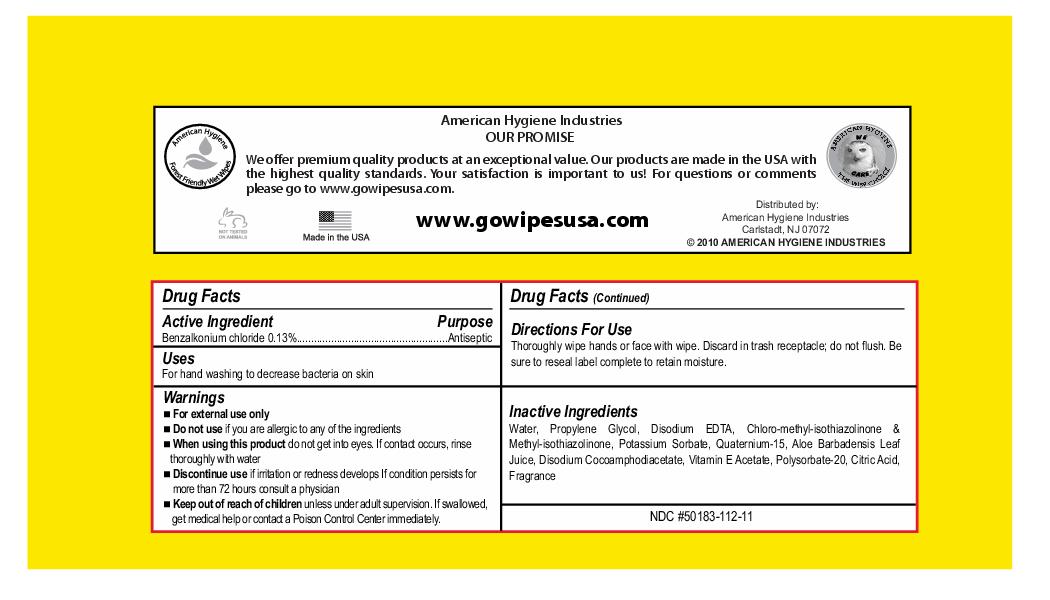 DRUG LABEL: go wipes
NDC: 50183-112 | Form: CLOTH
Manufacturer: American Hygiene Industries
Category: otc | Type: HUMAN OTC DRUG LABEL
Date: 20100708

ACTIVE INGREDIENTS: benzalkonium chloride 3.480 g/34.8 g

go wipes

Uses

For hand washing to decrease bacteria on skin

Active Ingredient Purpose
Benzalkonium Chloride 0.13% Antiseptic

Warnings

- For external use only
- Do not use if you are allergic to any of the ingredients
- When using this product do not get into eyes. If contact occurs, rinse thoroughly with water.
- Discontinue use if irritation or redness develops if condition persists for more than 72 hours consult a physician
- Keep out of reach of children unless under adult supervision. If swallowed get medical help or contact a Poison Control Center immediately.

INDICATIONS AND USAGE

Directions for use

Thoroughly wipe hands or face with wipe. Discard in trash receptacle; do not flush. Be sure to reseal label complete to retain moisture.

PACKAGE LABEL

American Hygiene

go anywhere wipes

Antibacterial skin sanitizing wipes

kills 99.99% germs

safe on hands and face

non sticky formula with vitamin e and aloe

thick strong 5" x 8" wipe

Join the movement

10 wet wipes

resealable pull tab